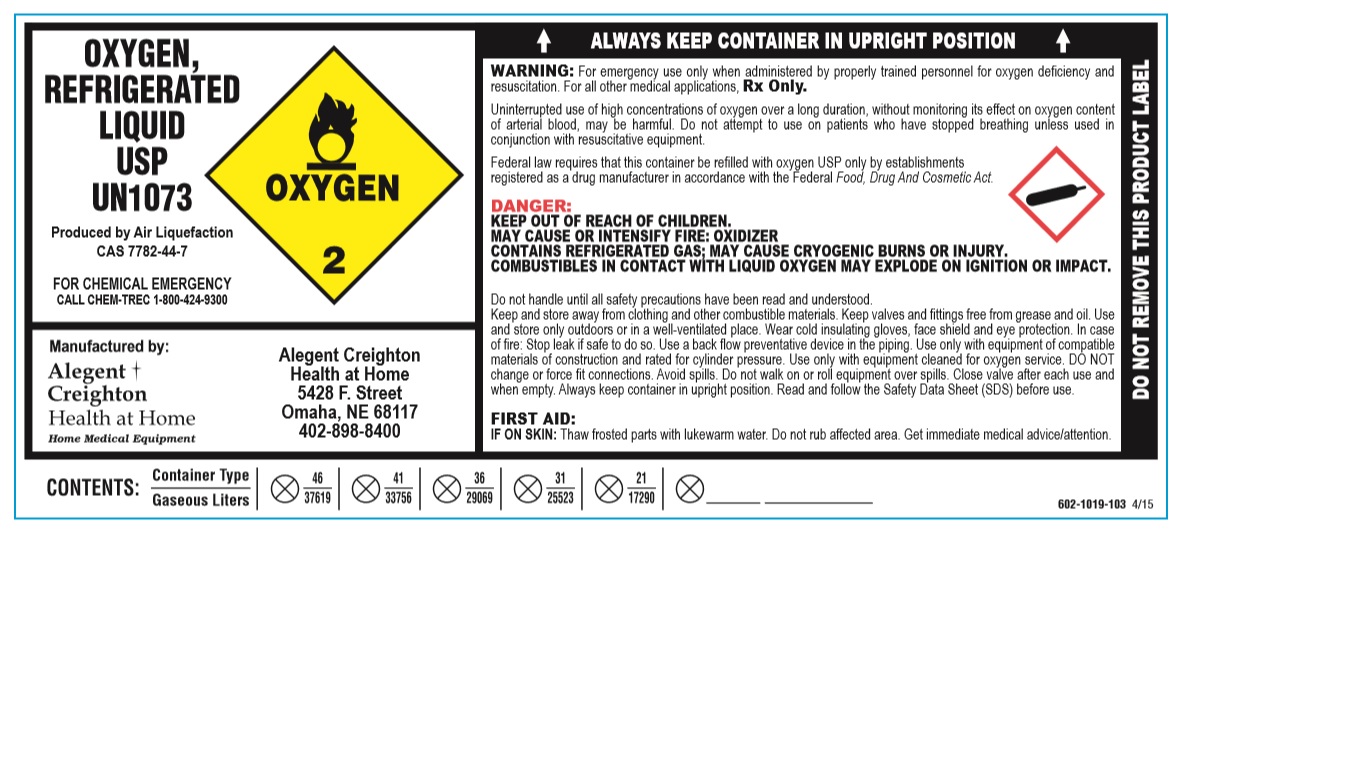 DRUG LABEL: Oxygen
NDC: 11110-0002 | Form: GAS
Manufacturer: Alegent Health
Category: prescription | Type: HUMAN PRESCRIPTION DRUG LABEL
Date: 20181204

ACTIVE INGREDIENTS: OXYGEN 99.1 L/1 L

oxygen

PACKAGE LABEL

OXYGEN, REFRIGERATED LIQUID USP

UN1073

Produced by Air Liquefaction

CAS 7782-44-7

FOR CHEMICAL EMERGENCY

CALL CHEM-TREC 1-800-424-9300

Manufactured by:

Alegent Creighton Health at Home

Home Medical Equipment

Alegent Creighton Health at Home

5428 F. Street

Omaha, NE 68117

402-898-8400

ALWAYS KEEP CONTAINER IN UPRIGHT POSITION

WARNING: For emergency use only when administered by properly trained personnel for oxygen deficiency and resuscitation. For all other medical applications, Rx Only.

Uninterrupted use of high concentrations of oxygen over a long duration, without monitoring its effect on oxygen content of arterial blood, may be harmful. Do not attempt to use on patients who have stopped breathing unless used in conjunction with resuscitative equipment.

Federal law requires that this container be refilled with oxygen USP only by establishments registered as a drug manufacturer in accordance with the Federal Food, Drug and Cosmetic Act.

DANGER:

KEEP OUT OF REACH OF CHILDREN.

MAY CAUSE OR INTENSIFY FIRE: OXIDIZER

CONTAINS REFRIGERATED GAS; MAY CAUSE CRYOGENIC BURNS OR INJURY.

COMBUSTIBLES IN CONTACT WITH LIQUID OXYGEN MAY EXPLODE ON IGNITION OR IMPACT.

Do not handle until all safety precautions have been read and understood.

Keep and store away from clothing and other combustible materials. Keep valves and fittings free from grease and oil. Use and store only outdoors or in a well-ventilated place. Wear cold insulating gloves, face shield and eye protection. In case of fire: Stop leak if safe to do so. Use a back flow preventive device in the piping. Use only with equipment of compatible materials of construction and rated for cylinder pressure. Use only with equipment cleaned for oxygen service. DO NOT change or force fit connections. Avoid spills. Do not walk on or roll equipment over spills. Close valve after each use and when empty. Always keep container in upright position. Read and follow the Safety Data Sheet (SDS) before use.

FIRST AID:

IF ON SKIN: Thaw frosted parts with lukewarm water. Do not rub affected area. Get immediate medical advice/attention.